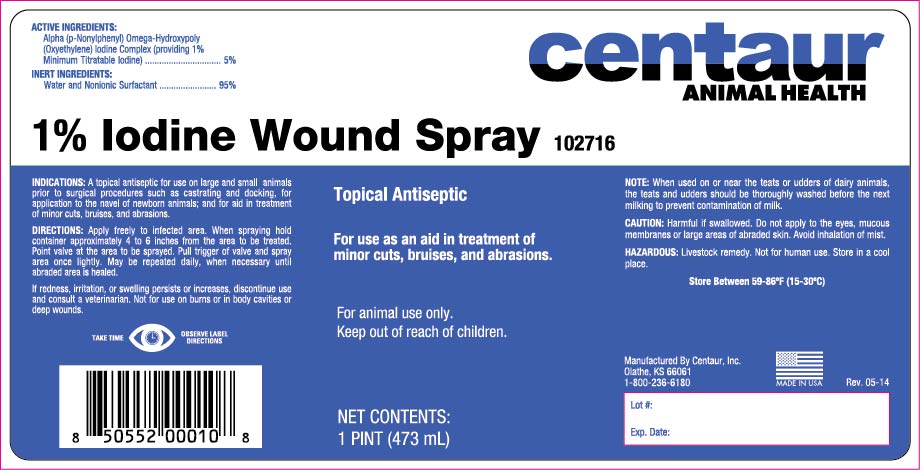 DRUG LABEL: 1% Iodine Wound
NDC: 58305-027 | Form: SOLUTION
Manufacturer: Centaur Inc
Category: animal | Type: OTC ANIMAL DRUG LABEL
Date: 20170824

ACTIVE INGREDIENTS: IODINE 0.01 mg/1 mL
INACTIVE INGREDIENTS: WATER 0.99 mg/1 mL

WARNINGS AND PRECAUTIONS

Topical Antiseptic
For animal use only.
Keep out of reach of children.

INDICATIONS
For use in horses, cattle, swine and sheep as a topical antiseptic for use prior to surgical procedures such as castrating and tail docking; for application to the umbilical stump (navel) of newborn animals; and for the aid in the treatment of minor cuts, bruises, teat sores, and abrasions

DIRECTIONS
Remove spray cap from 16 oz. container and refill from gallon container. Replace spray cap tightly. Hold container approxiamately 4 to 6 inches from the area to be sprayed. Point valve at the area to be sprayed. Pull trigger and spray area once lightly. May be repeated daily, when necessary, until abraded area is healed. Apply to the umbilical stump of newborns 2-3 times per day until stump has dried.
When using prior to surgical procedures, allow 10 minutes contact time.
CAUTION
If redness, irritation, or swelling persists or increases discontinue use and consult a veterinarian. Not for use on burns or in body cavities or deep wounds.
NOTE
When used on or near the teats or udders of dairy animals, the teats and udders should be thoroughly washed before the next milking to prevent contamination of milk.
Active Ingredients
Alpha (p-nonylphenyl) Omega-Hydroxypoly (Oxyethylene) Iodine Complex (providing 1% titratable Iodine) .................................. 5%
Inert Ingredients
Water & Nonionic Surfactant ................................. 95%
CAUTION
Harmful or fatal if swallowed. Do not apply to the eyes, mucous membranes or large areas of abraded skin. Avoid inhalation of mist.

KEEP TIGHTLY CLOSED WHEN NOT IN USE.
FOR EXTERNAL ANIMAL USE ONLY.
KEEP OUT REACH OF CHILDREN.
STORE AT 15o-30oC (59o-86oF)